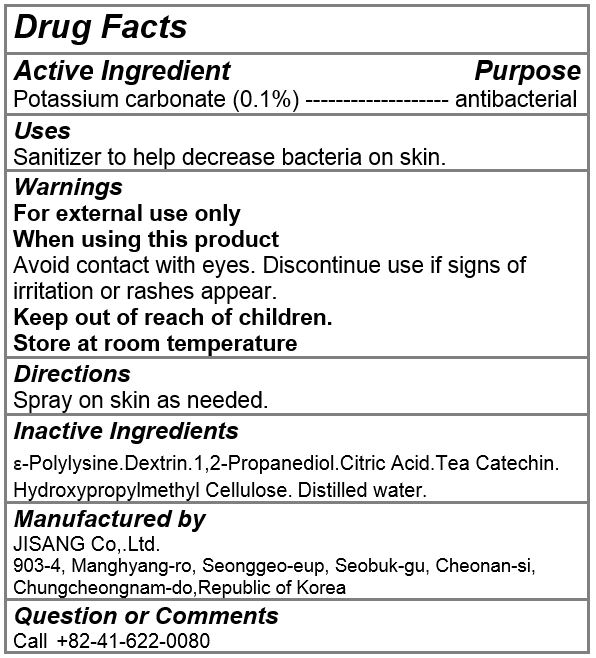 DRUG LABEL: ZEROQ
NDC: 80643-0002 | Form: LIQUID
Manufacturer: JISANG Co., Ltd.
Category: otc | Type: HUMAN OTC DRUG LABEL
Date: 20200928

ACTIVE INGREDIENTS: POTASSIUM CARBONATE 0.5 g/500 mL
INACTIVE INGREDIENTS: PROPYLENE GLYCOL; CITRIC ACID MONOHYDRATE; HYPROMELLOSE, UNSPECIFIED; WATER

ACTIVE INGREDIENT

potassium carbonate

INACTIVE INGREDIENT

e-polylysine, dextrin, 1,2-propanediol, citric acid, tea catechin, hydroxypropylmethyl cellulose, water

PURPOSE

Sanitizer to help decrease bacteria on skin

keep out of reach of the children

INDICATIONS AND USAGE

Spray on skin as needed

WARNINGS

For external use only.

When using this product

Avoid contact with eyes. Discontinue use if signs of irritation or rashes appear.

Keep out of reach of children.

Store at room temperature.

DOSAGE AND ADMINISTRATION

for external use only